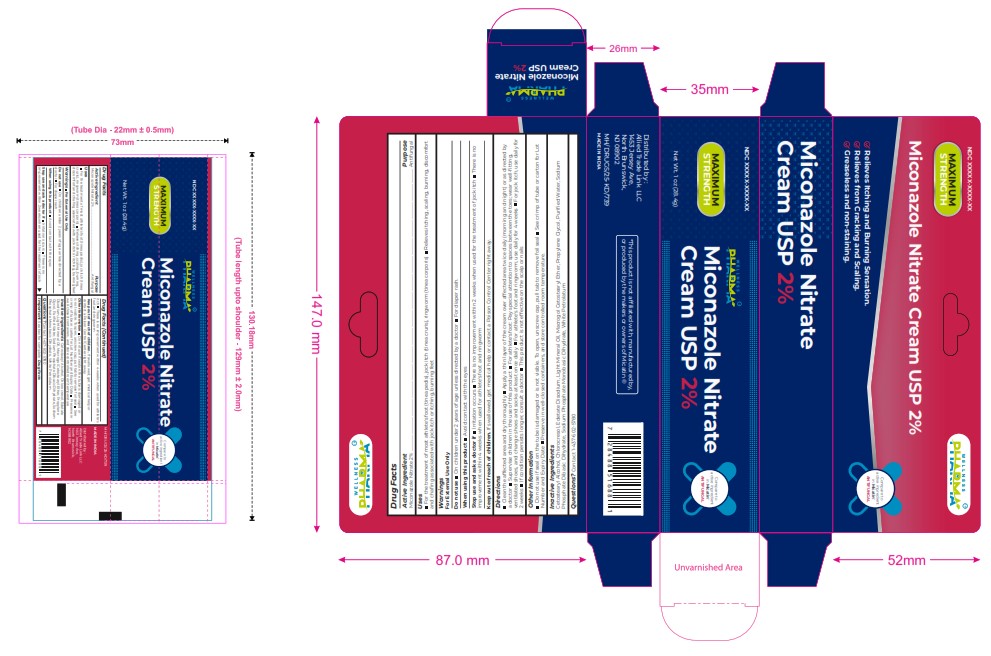 DRUG LABEL: MICONAZOLE NITRATE
NDC: 84387-003 | Form: OINTMENT
Manufacturer: ALLIED TRADE LINK LLC
Category: otc | Type: HUMAN OTC DRUG LABEL
Date: 20241112

ACTIVE INGREDIENTS: MICONAZOLE NITRATE 20 mg/1 g
INACTIVE INGREDIENTS: CETOSTEARYL ALCOHOL; CHLOROCRESOL; CETEARETH-12; 2-PHENYLPROPANAL PROPYLENE GLYCOL ACETAL; SODIUM PHOSPHATE DIBASIC DIHYDRATE; SODIUM PHOSPHATE, MONOBASIC, ANHYDROUS; LIGHT MINERAL OIL; WATER; WHITE PETROLATUM; EDETATE DISODIUM

Miconazole Nitrate

Uses

For the treatment of most athlete's foot (tinea pedis), jock itch (tinea cruris), ringworm (tinea corporis) Relieves itching, scaling, burning, discomfort
and chaﬁng associated with jock itch or itching, burning feet

Warnings For External Use Only

Do not use On children under 2 years of age unless directed by a doctor For diaper rash.
When using this product Avoid contact with the eyes
Stop use and ask a doctor if Irritation occurs There is no improvement within 2 weeks when used for the treatment of jock itch There is no
improvement within 4 weeks when used for athlete's foot and ringworm
Keep out of reach of children. If swallowed, get medical help or contact a Poison Control Center right away.

Do not use On children under 2 years of age unless directed by a
doctor For diaper rash.

When using this product Avoid contact with the eyes

Stop use and ask a doctor if Irritation occurs There is no
improvement within 2 weeks when used for the treatment of jock

itch There is no improvement within 4 weeks when used for athlete's
foot and ringworm

Keep out of reach of children. If swallowed, get medical help or
contact a Poison Control Center right away.

Other Information

Do not use if seal on the tube is damaged or
is not visible. To open, unscrew cap, pull tab to remove foil seal See
crimp of tube or carton for Lot Number and Expiry Date Preserve in
well-closed containers, and store controlled room temperature

Inactive Ingredients

Inactive Ingredients Cetostearyl Alcohol, Chlorocresol, Edetate
Disodium, Light Mineral Oil, Macrogol Cetostearyl Ether, Propylene
Glycol, Puriﬁed Water, Sodium Phosphate Dibasic Dihydrate, Sodium
Phosphate Monobasic Dihydrate, White Petrolatum

Active Ingrediant

Miconazole Nitrate 2%

WARNINGS FOR EXTERNAL USE ONLY

Miconazole Nitrate 2%

For External Use Only
Do not use On children under 2 years of age unless directed by a doctor For diaper rash.
When using this product Avoid contact with the eyes
Stop use and ask a doctor if Irritation occurs There is no improvement within 2 weeks when used for the treatment of jock itch There is no
improvement within 4 weeks when used for athlete's foot and ringworm
Keep out of reach of children. If swallowed, get medical help or contact a Poison Control Center right away.

DIRECTIONS AND USES

Uses
For the treatment of most athlete's foot (tinea pedis), jock itch (tinea cruris), ringworm (tinea corporis) Relieves itching, scaling, burning, discomfort
and chaﬁng associated with jock itch or itching, burning feet

Clean the affected area and dry thoroughly Apply a thin layer of the cream over affected area twice daily (morning and night) or as directed by
a doctor Supervise children in the use of this product For athlete's foot: Pay special attention to spaces between the toes; wear well-ﬁtting,
ventilated shoes, and change shoes and socks at least once daily For athlete's foot and ringworm, use daily for 4 weeks For jock itch, use daily for
2 weeks If condition persists longer, consult a doctor This product is not effective on the scalp or nails

PURPOSDE

Miconazole Nitrate 2% ........................................................................................................................................................................................................................................................................... Antifungal